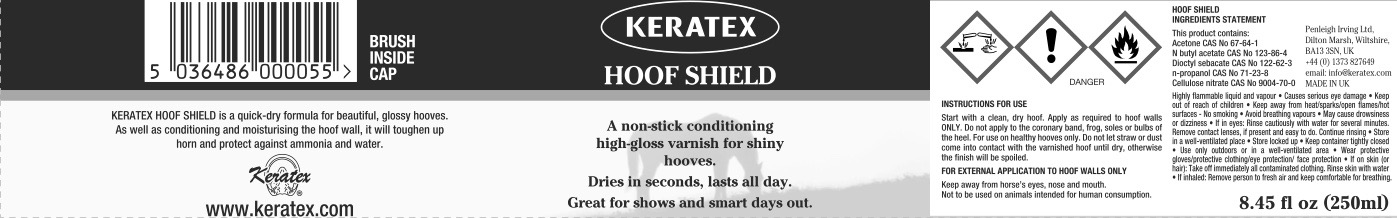 DRUG LABEL: Keratex
NDC: 27426-050 | Form: LIQUID
Manufacturer: Penleigh Irving Ltd
Category: animal | Type: OTC ANIMAL DRUG LABEL
Date: 20181220

ACTIVE INGREDIENTS: BUTYL ACETATE 0.088 g/1 mL; DIETHYLHEXYL SEBACATE 0.046 g/1 mL; PYROXYLIN 0.13 g/1 mL

SAFE HANDLING WARNING

Highly flammable liquid and vapour. Causes serious eye damage. Keep out of reach of children. Keep away from heat/sparks/open flames/hot surfaces. No smoking. Avoid breathing vapours. May cause drowsiness and dizziness. If in eyes: Rinse cautiously with water for several minutes. Remove contact lenses if present and easy to do. Continue rinsing. Store in a well-ventilated place. Store locked up. Keep container tightly closed. Use only outdoors or in a well-ventilated area. Wear protective gloves/protective clothing/eye protection/face protection. If on skin (or hair): Take off immediately all contaminated clothing. Rinse skin with water. If inhaled: Remove person to fresh air and keep comfortable for breathing.

PACKAGE LABEL

Keratex Hoof Shield

A conditioning high-gloss varnish for shiny hooves.

Dries in seconds, lasts all day.

Great for shows and smart days out.

Keratex Hoof Shield is a quick-dry formula for beautiful, glossy hooves. As well as conditioning and moisturizing the hoof wall, it will toughen up horn and protect against ammonia and water.

Instructions for use: Start with a clean, dry hoof. Apply as required to hoof walls only. Do not apply to the coronary band, frog, soles or bulbs of the heel. For use on healthy hooves only. Do not let straw or dust come into contact with the varnished hoof until dry, otherwise the finish will be spoiled.

For External Application To Hoof Walls Only

Keep away from horse's eyes, nose and mouth. Not to be used on animals intended for human consumption.

Hoof Shield Ingredients Statement This product contains: Acetone CAS No. 67-64-1. N butyl acetate CAS No. 123-86-4. Dioctyl sebacate CAS No. 122-62-3. N-propanol CAS No. 71-23-8. Cellulose nitrate CAS No. 9004-70-0.

8.45 fl oz (250 ml) Brush Inside Cap

MADE IN UK

Penleigh Irving Ltd.

Dilton Marsh, Wiltshire, BK13 3SN, UK

+44 (0) 1373 827649 email: info@keratex.com

www.keratex.com